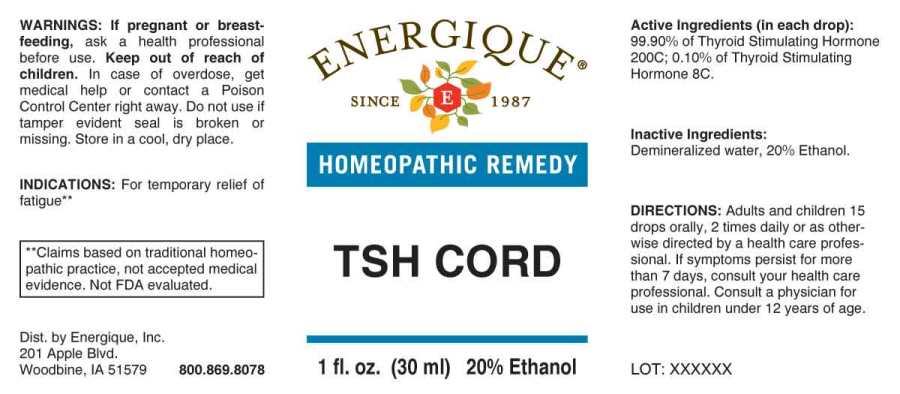 DRUG LABEL: TSH Cord
NDC: 44911-0307 | Form: LIQUID
Manufacturer: Energique, Inc.
Category: homeopathic | Type: HUMAN OTC DRUG LABEL
Date: 20240712

ACTIVE INGREDIENTS: THYROTROPIN 8 [hp_C]/1 mL
INACTIVE INGREDIENTS: WATER; ALCOHOL

DRUG FACTS:

ACTIVE INGREDIENTS:

(in each drop): 99.90% of Thyroid Stimulating Hormone 200C; 0.10% of Thyroid Stimulating Hormone 8C.

INDICATIONS:

For temporary relief of fatigue**

**Claims based on traditional homeopathic practice, not accepted medical evidence. Not FDA evaluated.

WARNINGS:

If pregnant or breast-feeding, ask a health professional before use.

Keep out of reach of children. In case of overdose, get medical help or contact a Poison Control Center right away.

Do not use if tamper evident seal is broken or missing.

Store in a cool, dry place.

KEEP OUT OF REACH OF CHILDREN:

In case of overdose, get medical help or contact a Poison Control Center right away.

DIRECTIONS:

Adults and children 15 drops orally, 2 times daily or as otherwise directed by a health care professional. If symptoms persist for more than 7 days, consult your health care professional. Consult a physician for use in children under 12 years of age.

INDICATIONS:

For temporary relief of fatigue**

**Claims based on traditional homeopathic practice, not accepted medical evidence. Not FDA evaluated.

INACTIVE INGREDIENTS:

Demineralized water, 20% Ethanol.

QUESTIONS:

Dist. By Energique, Inc.

201 Apple Blvd.

Woodbine, IA 51579 800.869.8078

PACKAGE DISPLAY LABEL:

ENERGIQUE

SINCE 1987

HOMEOPATHIC REMEDY

TSH CORD

1 fl. oz. (30 ml)